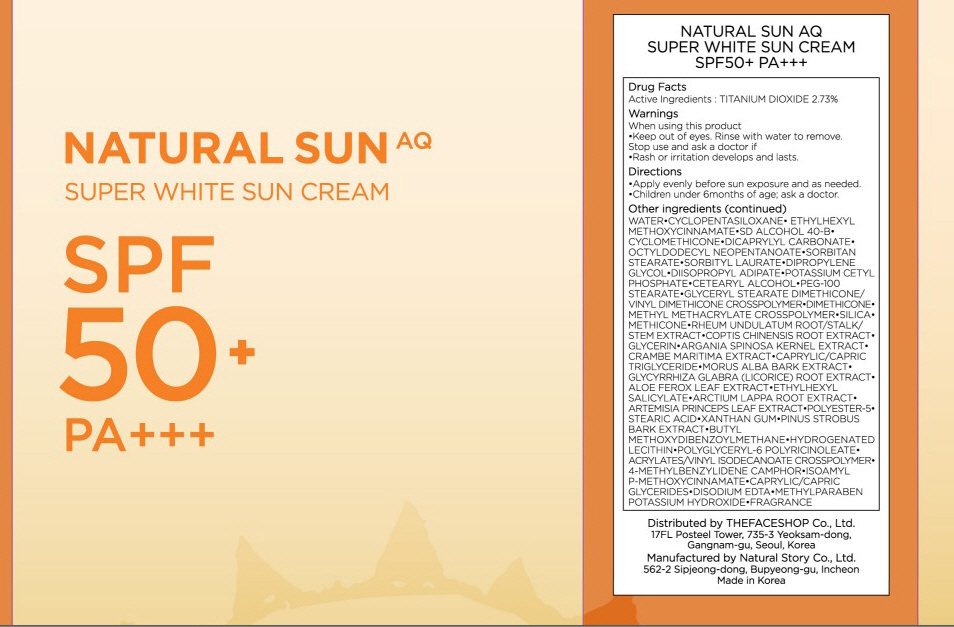 DRUG LABEL: NATURAL SUN AQ SUPER WHITE SUN
NDC: 51523-022 | Form: CREAM
Manufacturer: THEFACESHOP CO., LTD.
Category: otc | Type: HUMAN OTC DRUG LABEL
Date: 20100714

ACTIVE INGREDIENTS: TITANIUM DIOXIDE 1.36 mL/50 mL

Drug Facts

Active Ingredient: TITANIUM DIOXIDE

Inactive Ingredients:
WATER, CYCLOPENTASILOXANE, ETHYLHEXYL METHOXYCINNAMATE, SD ALCOHOL 40-B, CYCLOMETHICONE, DICAPRYLYL CARBONATE, OCTYLDODECYL NEOPENTANOATE, SORBITAN STEARATE, SORBITYL LAURATE, DIPROPYLENE, GLYCOL, DIISOPROPYL ADIPATE, POTASSIUM CETYL PHOSPHATE, CETEARYL ALCOHOL, PEG-100 STEARATE,
GLYCERYL STEARATE DIMETHICONE/VINYL DIMETHICONE CROSSPOLYMER, DIMETHICONE, METHYL METHACRYLATE CROSSPOLYMER, SILICA, METHICONE, RHEUM UNDULATUM ROOT/STALK/STEM EXTRACT, COPTIS CHINENSIS ROOT EXTRACT, GLYCERIN, ARGANIA SPINOSA KERNEL EXTRACT, CRAMBE MARITIMA EXTRACT, CAPRYLIC/CAPRIC TRIGLYCERIDE, MORUS ALBA BARK EXTRACT, GLYCYRRHIZA GLABRA (LICORICE) ROOT EXTRACT, ALOE FEROX LEAF EXTRACT, ETHYLHEXYL SALICYLATE, ARCTIUM LAPPA ROOT EXTRACT, ARTEMISIA PRINCEPS LEAF EXTRACT, POLYESTER-5, STEARIC ACID, XANTHAN GUM, PINUS STROBUS BARK EXTRACT, BUTYL METHOXYDIBENZOYLMETHANE, HYDROGENATED LECITHIN, POLYGLYCERYL-6 POLYRICINOLEATE, ACRYLATES/VINYL ISODECANOATE CROSSPOLYMER, 4-METHYLBENZYLIDENE CAMPHOR, ISOAMYL P-METHOXYCINNAMATE, CAPRYLIC/CAPRIC GLYCERIDES, DISODIUM EDTA, METHYLPARABEN POTASSIUM HYDROXIDE, FRAGRANCE

Warnings:
When using this product
Keep out of eyes. Rinse with water to remove.
Stop use and ask a doctor if
Rash or irritation develops and lasts.
Directions:
Apply evenly before sun exposure and as needed.
Children under 6months of age; ask a doctor.